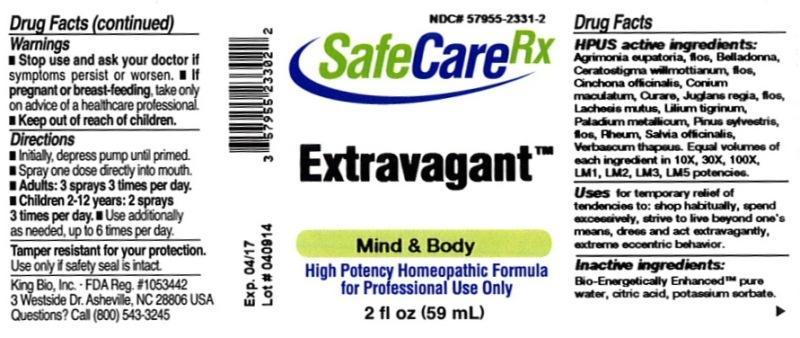 DRUG LABEL: Extravagant
NDC: 57955-2331 | Form: LIQUID
Manufacturer: King Bio Inc.
Category: homeopathic | Type: HUMAN OTC DRUG LABEL
Date: 20140422

ACTIVE INGREDIENTS: AGRIMONIA EUPATORIA FLOWER 10 [hp_X]/59 mL; ATROPA BELLADONNA 10 [hp_X]/59 mL; CERATOSTIGMA WILLMOTTIANUM FLOWER 10 [hp_X]/59 mL; CINCHONA OFFICINALIS BARK 10 [hp_X]/59 mL; CONIUM MACULATUM FLOWERING TOP 10 [hp_X]/59 mL; TUBOCURARINE CHLORIDE 10 [hp_X]/59 mL; JUGLANS REGIA FLOWERING TOP 10 [hp_X]/59 mL; LACHESIS MUTA VENOM 10 [hp_X]/59 mL; LILIUM LANCIFOLIUM WHOLE FLOWERING 10 [hp_X]/59 mL; PALLADIUM 10 [hp_X]/59 mL; PINUS SYLVESTRIS FLOWERING TOP 10 [hp_X]/59 mL; RHEUM OFFICINALE ROOT 10 [hp_X]/59 mL; SAGE 10 [hp_X]/59 mL; VERBASCUM THAPSUS 10 [hp_X]/59 mL
INACTIVE INGREDIENTS: WATER; CITRIC ACID MONOHYDRATE; POTASSIUM SORBATE

Extravagant™

ACTIVE INGREDIENT

Drug Facts__________________________________________________________________________________________________________

HPUS activeingredients: Agrimonia eupatoria, flos, Belladonna, Ceratostigma willmottianum, flos, Cinchona officinalis, Conium maculatum, Curare, Juglans Regia, flos, Lachesis mutus, Lilium tigrinum, Palladium metallicum, Pinus sylvestris, flos, Rheum, Salvia officinalis, Verbascum thapsus. Equal volumes of each ingredient in 10X, 30X, 100X, LM1, LM2, LM3, LM5 potencies.

INDICATIONS AND USAGE

Uses for temporary relief of tendencies to: shop habitually, spend excessively, strive to live beyond one's means, dress and act extravagantly, extreme eccentric behavior.

Inactive Ingredients:

Bio-Energetically Enhanced™ pure water, citric acid and potassium sorbate.

Warnings

- Stop use and ask your doctor if symptoms persist or worsen.
- If pregnant or breast-feeding, take only on advice of a healthcare professional.

- Keep out of reach of children.

Directions

- Initially, depress pump until primed.
- Spray one dose directly into mouth.
- Adults: 3 sprays 3 times per day.
- Children 2-12 years: 2 sprays 3 times per day.
- Use additionally as needed, up to 6 times per day.

OTHER SAFETY INFORMATION

Tamper resistant for your protection. Use only if safety seal is intact.

PURPOSE

Uses for temporary relief of tendencies to:

- shop habitually
- spend excessively
- strive to live beyond one's means
- dress and act extravagantly
- extreme eccentric behavior